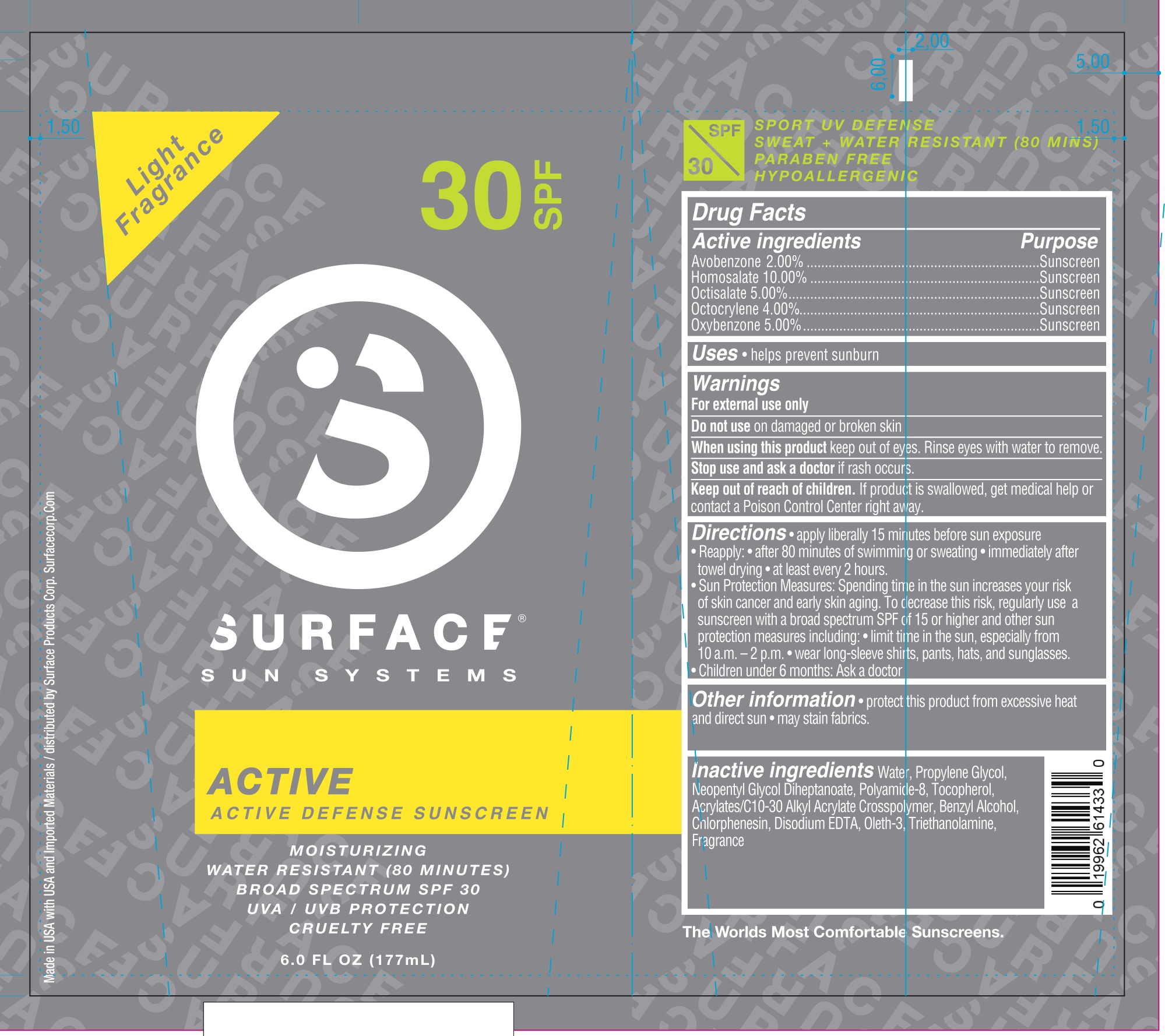 DRUG LABEL: Surface Sun Active Defense SPF 30 Sunscreen
NDC: 72344-007 | Form: LOTION
Manufacturer: Surface Products Corp
Category: otc | Type: HUMAN OTC DRUG LABEL
Date: 20180525

ACTIVE INGREDIENTS: AVOBENZONE 2 g/100 mL; HOMOSALATE 10 g/100 mL; OCTISALATE 5 g/100 mL; OXYBENZONE 5 g/100 mL; OCTOCRYLENE 10 g/100 mL
INACTIVE INGREDIENTS: EDETATE DISODIUM; WATER; PROPYLENE GLYCOL; NEOPENTYL GLYCOL DIHEPTANOATE; TOCOPHEROL; TROLAMINE; OLETH-3; ALCOHOL; GLYCERIN; ACRYLATE/ISOBUTYL METHACRYLATE/N-TERT-OCTYLACRYLAMIDE COPOLYMER (75000 MW); POLYAMIDE-8 (4500 MW); CARBOMER INTERPOLYMER TYPE A (55000 CPS); BENZYL ALCOHOL; CHLORPHENESIN

Active Ingredients

Avobenzone 2%, Homosalate 10%, Octisalate 5%, Octocrylene 4%, Oxybenzone 5%

Purpose

Sunscreen

Use

Helps prevent sunburn.

Warnings

For external use only.

Do not use on damaged or broken skin. When using this product keep out of eyes. Rinse eyes with water to remove. Stop use and ask a doctor if rash occurs.

Keep Out of Reach of Children.

If product is swallowed, get medical help or contact a Poison Control Center right away.

Directions

Apply liberally 15 minutes before sun exposure. Reapply:

- after 80 minutes of swimming or sweating
- immediately after towel drying
- at least every 2 hours.

Sun Protection Measures: Spending time in the sun increases your risk of skin cancer and early skin aging. To decrease this risk, regularly use a sunscreen with a broad spectrum SPF of 15 or higher and other sun protection measures including:

- Limit time in the sun, especially from 10 a.m. - 2 p.m.
- Wear long-sleeved shirts, pants, hats, and sunglasses.

Children under 6 months: ask a doctor.

Inactive Ingredients

Water, Propylene Glycol, Neopentyl Glycol Diheptanoate, Polyamide-8, Tocopherol, Acrylates/C10-30 Alkyl Acrylate Crosspolymer, Benzyl Alcohol, Chlorphenesin, Disodium EDTA, Oleth-3, Triethanolamine, Fragrance.